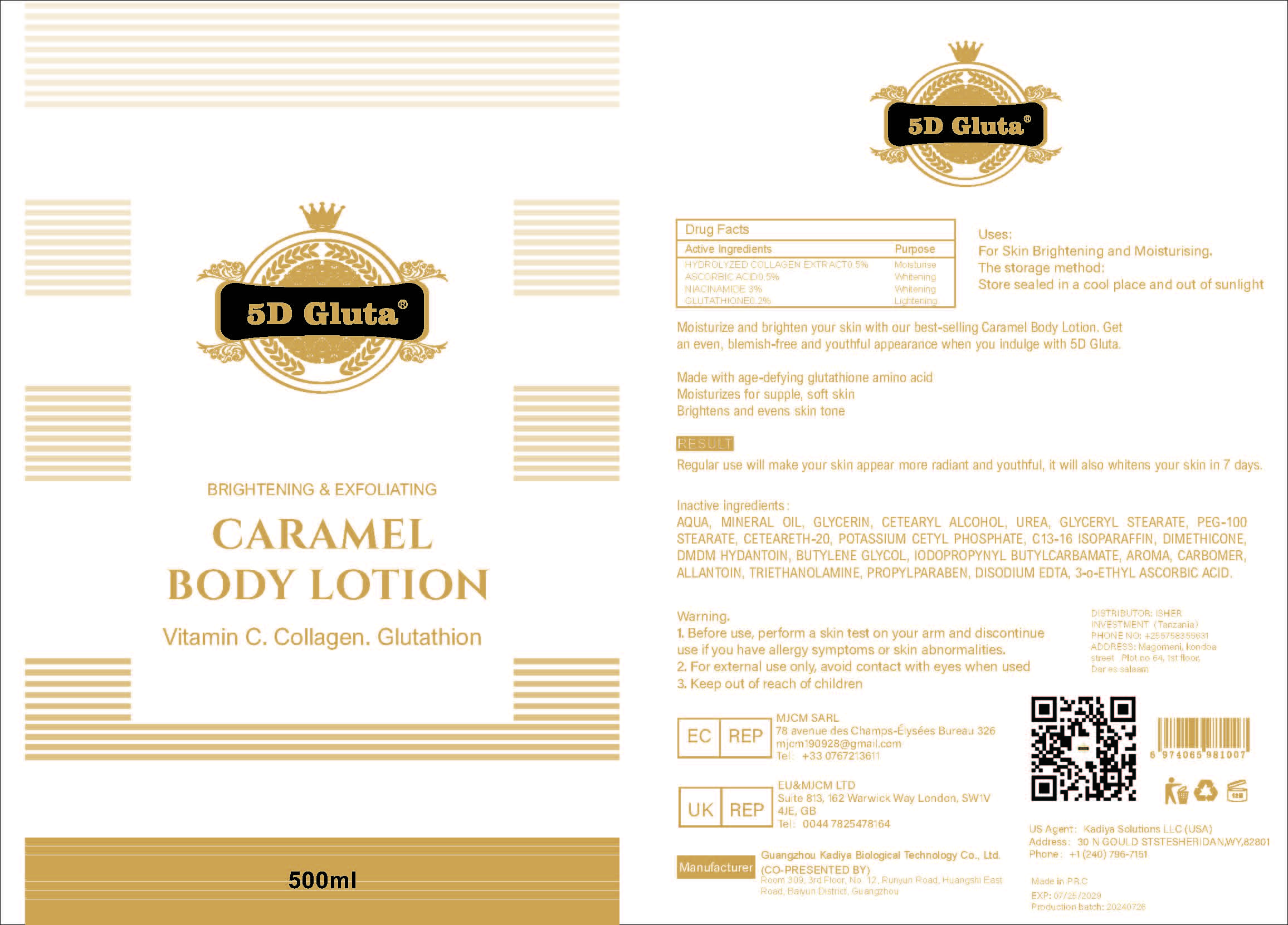 DRUG LABEL: CaramelBodyLotion
NDC: 84423-056 | Form: CREAM
Manufacturer: Guangzhou Kadiya Biotechnology Co., Ltd.
Category: otc | Type: HUMAN OTC DRUG LABEL
Date: 20241217

ACTIVE INGREDIENTS: GLUTATHIONE 1 g/500 mL; NIACINAMIDE 15 g/500 mL; ASCORBIC ACID 2.5 g/500 mL
INACTIVE INGREDIENTS: POTASSIUM CETYL PHOSPHATE; PROPYLPARABEN; CETEARETH-20; C13-16 ISOPARAFFIN; DMDM HYDANTOIN; IODOPROPYNYL BUTYLCARBAMATE; CARBOMER; ALLANTOIN; TRIETHANOLAMINE; EDETATE DISODIUM; 3-O-ETHYL ASCORBIC ACID; PEG-100 STEARATE; AQUA; GLYCERIN; UREA; MINERAL OIL; GLYCERYL STEARATE; DIMETHICONE 1000; CETEARYL ALCOHOL; BUTYLENE GLYCOL

PURPOSE

For Skin Brightening and Moisturising

INACTIVE INGREDIENT

AQUA、MINERAL OIL、GLYCERIN、CETEARYL ALCOHOL、UREA、GLYCERYL STEARATE、PEG-100 STEARATE、CETEARETH-20、POTASSIUM CETYL PHOSPHATE、C13-16 ISOPARAFFIN、DIMETHICONE、DMDM HYDANTOIN、BUTYLENE GLYCOL、IODOPROPYNYL BUTYLCARBAMATE、AROMA、CARBOMER、ALLANTOIN、TRIETHANOLAMINE、PROPYLPARABEN、DISODIUM EDTA、3-o-ETHYL ASCORBIC ACID

WARNINGS

1.Before use, perform a skin test on your arm and discontinue use if you have allergy symptoms or skin abnormalities.
2、For external use only, avoid contact with eyes when used
3、Keep out of reach of children

INDICATIONS AND USAGE

Moisturize and brighten your skin with our best-selling Caramel Body Lotion. Get an even, blemish-free and youthful appearance when you indulge with 5D Gluta. Made with age-defying glutathione amino acicMoisturizes for supple, soft skinBrightens and evens skin tone

DOSAGE AND ADMINISTRATION

Regular use will make your skin appear more radiant and youthful, it will also whitens your skin in 7 days.

KEEP OUT OF REACH OF CHILDREN SECTION

Active Ingredients Purpose
HYDROLYZED COLLAGEN EXTRACT0.5% Moisturise
ASCORBIC ACID0.5% Whitening
NIACINAMIDE 3% Whitening
GLUTATHIONE0.2% Lightening

PACKAGE LABEL

Active Ingredients Purpose
HYDROLYZED COLLAGEN EXTRACT0.5% Moisturise
ASCORBIC ACID0.5% Whitening
NIACINAMIDE 3% Whitening
GLUTATHIONE0.2% Lightening

Uses：
For Skin Brightening and Moisturising
The storage method：
Store sealed in a cool place and out of sunlight

Warning.
1.Before use, perform a skin test on your arm and discontinue use if you have allergy symptoms or skin abnormalities.
2、For external use only, avoid contact with eyes when used
3、Keep out of reach of children

Inactive ingredients：
AQUA、MINERAL OIL、GLYCERIN、CETEARYL ALCOHOL、UREA、GLYCERYL STEARATE、PEG-100 STEARATE、CETEARETH-20、POTASSIUM CETYL PHOSPHATE、C13-16 ISOPARAFFIN、DIMETHICONE、DMDM HYDANTOIN、BUTYLENE GLYCOL、IODOPROPYNYL BUTYLCARBAMATE、AROMA、CARBOMER、ALLANTOIN、TRIETHANOLAMINE、PROPYLPARABEN、DISODIUM EDTA、3-o-ETHYL ASCORBIC ACID